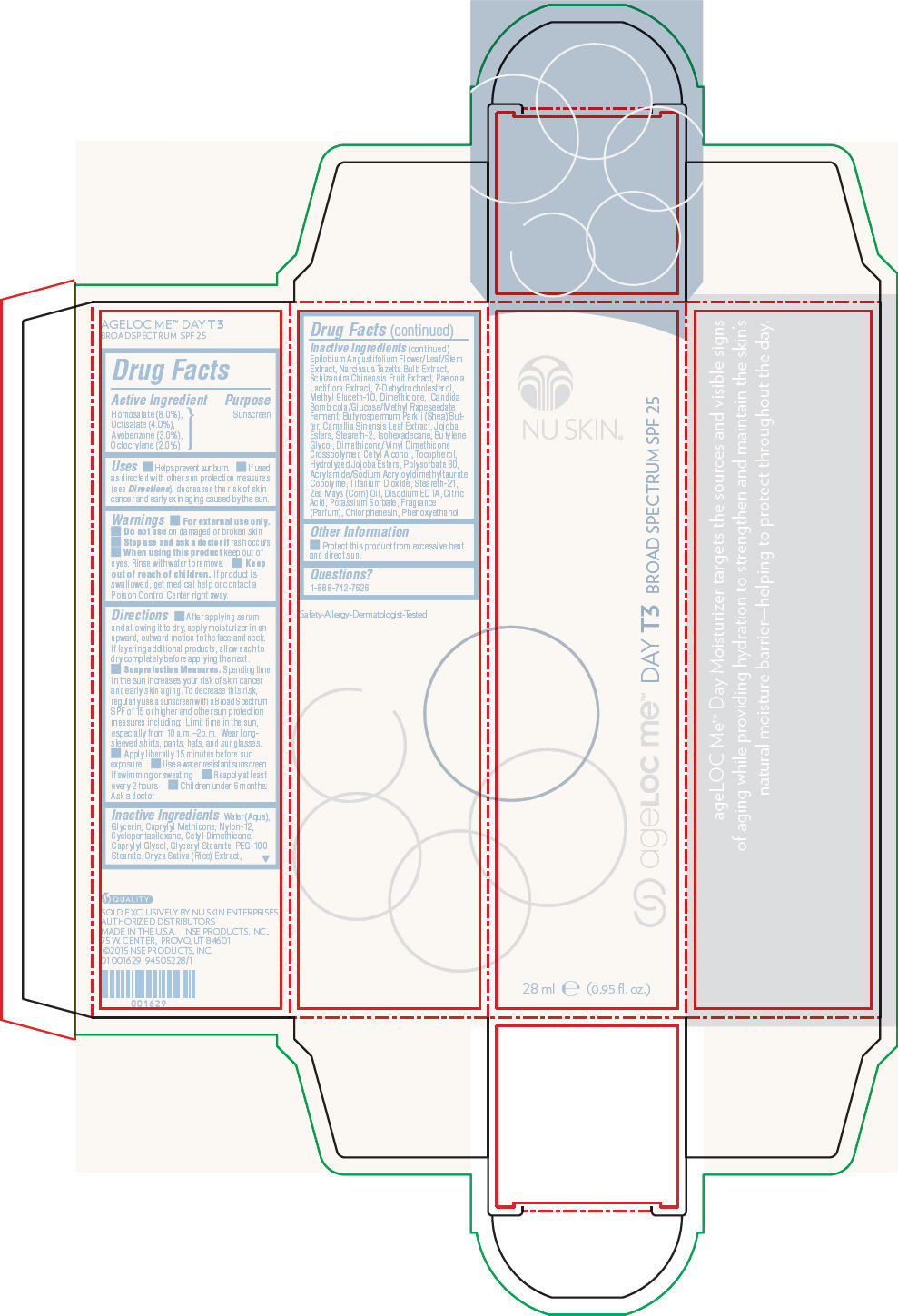 DRUG LABEL: Nu Skin ageLOC Me Day T3 Broad Spectrum SPF 25
NDC: 62839-1629 | Form: LOTION
Manufacturer: NSE Products, Inc.
Category: otc | Type: HUMAN OTC DRUG LABEL
Date: 20220111

ACTIVE INGREDIENTS: Homosalate 80 mg/1 mL; Octisalate 40 mg/1 mL; Avobenzone 30 mg/1 mL; Octocrylene 20 mg/1 mL
INACTIVE INGREDIENTS: Water; Glycerin; Caprylyl Trisiloxane; Cyclomethicone 5; Caprylyl Glycol; Glyceryl Monostearate; PEG-100 Stearate; Cetyl Alcohol; Steareth-3; Steareth-22; Isohexadecane; Dimethicone; Butylene Glycol; Rice Germ; Phenoxyethanol; Chlorphenesin; Hydrolyzed Jojoba Esters (Acid Form); Polysorbate 80; Shea Butter; Titanium Dioxide; Edetate Disodium; Green Tea Leaf; Epilobium Angustifolium Flowering Top; Citric Acid Monohydrate; Schisandra Chinensis Fruit; Corn Oil; Potassium Sorbate; Narcissus Tazetta Bulb; 7-Dehydrocholesterol; Tocopherol

Nu Skin® ageLOC Me™ Day T3 Broad Spectrum SPF 25

Drug Facts

Active Ingredient

Homosalate (8.0%),
Octisalate (4.0%),
Avobenzone (3.0%),
Octocrylene (2.0%)

Purpose

Sunscreen

Uses

- Helps prevent sunburn.
- If used as directed with other sun protection measures (see Directions), decreases the risk of skin cancer and early skin aging caused by the sun.

Warnings

- For external use only.

- Do not use on damaged or broken skin

- Stop use and ask a doctor if rash occurs

- When using this product keep out of eyes. Rinse with water to remove.

- Keep out of reach of children. If product is swallowed, get medical help or contact a Poison Control Center right away.

Directions

- After applying serum and allowing it to dry, apply moisturizer in an upward, outward motion to the face and neck. If layering additional products, allow each to dry completely before applying the next.
- Sunprotection Measures. Spending time in the sun increases your risk of skin cancer and early skin aging. To decrease this risk, regularly use a sunscreen with a Broad Spectrum SPF of 15 or higher and other sun protection measures including: Limit time in the sun, especially from 10 a.m.–2p.m. Wear long-sleeved shirts, pants, hats, and sunglasses.
- Apply liberally 15 minutes before sun exposure
- Use a water resistant sunscreen if swimming or sweating
- Reapply at least every 2 hours
- Children under 6 months: Ask a doctor

Inactive Ingredients

Water (Aqua), Glycerin, Caprylyl Methicone, Nylon-12, Cyclopentasiloxane, Cetyl Dimethicone, Caprylyl Glycol, Glyceryl Stearate, PEG-100 Stearate, Oryza Sativa (Rice) Extract, Epilobium Angustifolium Flower/Leaf/Stem Extract, Narcissus Tazetta Bulb Extract, Schizandra Chinensis Fruit Extract, Paeonia Lactiflora Extract, 7-Dehydrocholesterol, Methyl Gluceth-10, Dimethicone, Candida Bombicola/Glucose/Methyl Rapeseedate Ferment, Butyrospermum Parkii (Shea) Butter, Camellia Sinensis Leaf Extract, Jojoba Esters, Steareth-2, Isohexadecane, Butylene Glycol, Dimethicone/Vinyl Dimethicone Crosspolymer, Cetyl Alcohol, Tocopherol, Hydrolyzed Jojoba Esters, Polysorbate 80, Acrylamide/Sodium Acryloyldimethyltaurate Copolyme, Titanium Dioxide, Steareth-21, Zea Mays (Corn) Oil, Disodium EDTA, Citric Acid, Potassium Sorbate, Fragrance (Parfum), Chlorphenesin, Phenoxyethanol

Other Information

- Protect this product from excessive heat and direct sun.

Questions?

1-888-742-7626

PRINCIPAL DISPLAY PANEL - 28 ml Cartridge Carton

NU SKIN®

ageLOC me™ DAY T3 BROAD SPECTRUM SPF 25

28 ml e (0.95 fl. oz.)